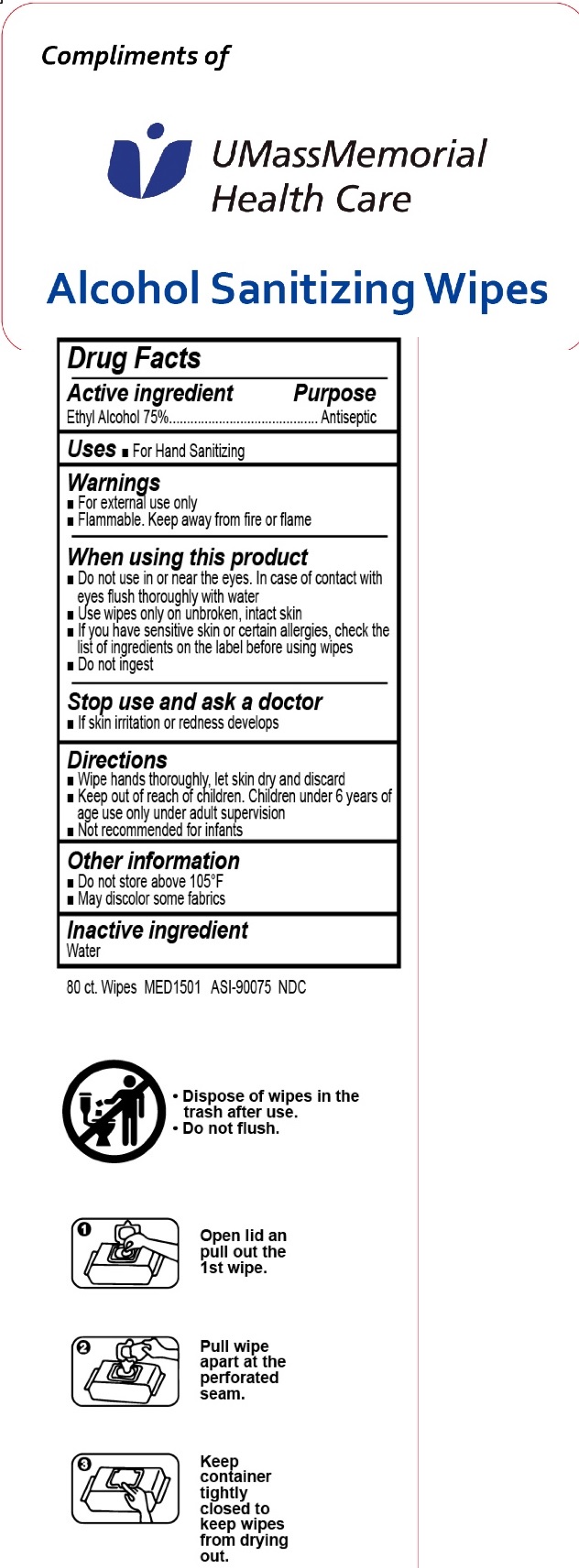 DRUG LABEL: Alcohol Sanitizing Wipes
NDC: 77909-006 | Form: CLOTH
Manufacturer: Zhejiang Huihao Daily Products Co.,Ltd
Category: otc | Type: HUMAN OTC DRUG LABEL
Date: 20200616

ACTIVE INGREDIENTS: ALCOHOL 75 g/100 g
INACTIVE INGREDIENTS: water

Wipes

Active Ingredient

ethyl Alcohol 75%

Purpose

Antiseptic

USES

- For hand Sanitizing

Warnings

- For external use only.
- Flammable, Keep away from fire or flame

When using this product,

- do not use in or near the eyes. In case of contact, rinse eyes thoroughly with water.
- Use wipes only on unbroken, intact skin
- if you have sensitive skin or certain allergies, check the list of ingredients on the label before using wipes
- Do not ingest

Stop use and ask a doctor If

- skin irritation or redness develops

KEEP OUT OF REACH OF CHILDREN

If swallowed, get medical help or contact a Poison Contrl Center right away.

Directions

- wipe hands thoroughly, let skin dry and discard
- keep out of reach of children. Children under 6 years of age use only under adult supervision
- Not recommended for infants

Other information:

- Do not store above 105℉
- May discolor some fabrics

Inactive ingredients

water